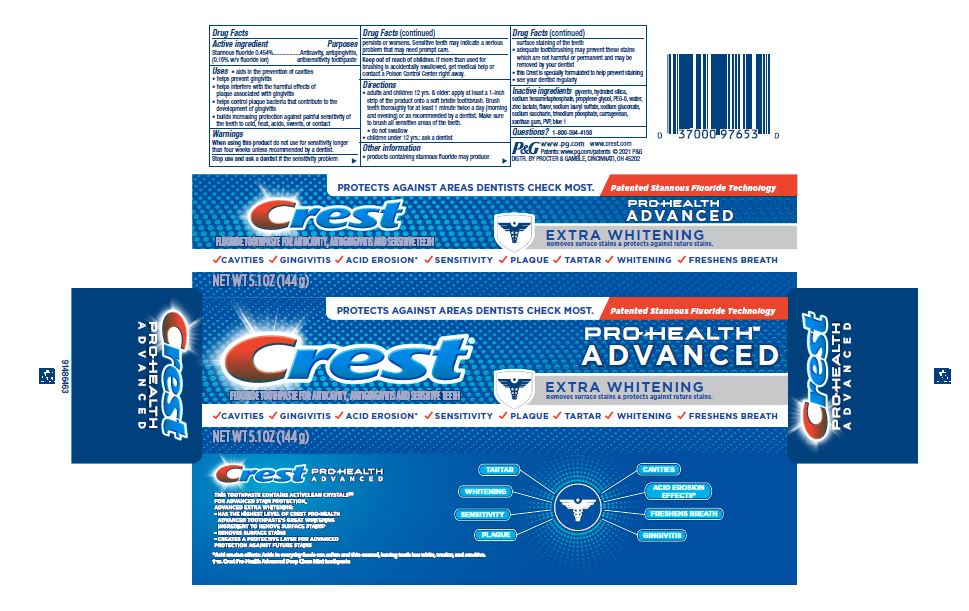 DRUG LABEL: Crest Pro-Health Advanced
NDC: 69423-938 | Form: GEL, DENTIFRICE
Manufacturer: The Procter & Gamble Manufacturing Company
Category: otc | Type: HUMAN OTC DRUG LABEL
Date: 20250108

ACTIVE INGREDIENTS: STANNOUS FLUORIDE 1.6 mg/1 g
INACTIVE INGREDIENTS: SODIUM PHOSPHATE, TRIBASIC, ANHYDROUS; POVIDONE, UNSPECIFIED; GLYCERIN; HYDRATED SILICA; SODIUM POLYMETAPHOSPHATE; PROPYLENE GLYCOL; POLYETHYLENE GLYCOL 300; WATER; ZINC LACTATE; SODIUM LAURYL SULFATE; SODIUM GLUCONATE; CARRAGEENAN; SACCHARIN SODIUM; XANTHAN GUM; FD&C BLUE NO. 1

Crest Pro Health Advanced Extra Whitening

Drug Facts

Active ingredient

Stannous fluoride 0.454%
(0.16% w/v fluoride ion)

Purposes

Anticavity, antigingivitis, antisensitivity toothpaste

Uses

- aids in the prevention of cavities
- helps prevent gingivitis
- helps interfere with the harmful effects of plaque associated with gingivitis
- helps control plaque bacteria that contribute to the development of gingivitis
- builds increasing protection against painful sensitivity of the teeth to cold, heat, acids, sweets, or contact

Warnings

When using this product do not use for sensitivity longer than four weeks unless recommended by a dentist.

Stop use and ask a dentist if the sensitivity problem persists or worsens. Sensitive teeth may indicate a serious problem that may need prompt care.

Keep out of reach of children. If more than used for brushing is accidentally swallowed, get medical help or contact a Poison Control Center right away.

Directions

- adults and children 12 yrs. & older: apply at least a 1-inch strip of the product onto a soft bristle toothbrush. Brush teeth thoroughly for at least 1 minute twice a day (morning and evening) or as recommended by a dentist. Make sure to brush all sensitive areas of the teeth.
- do not swallow
- children under 12 yrs.: ask a dentist

Other information

- products containing stannous fluoride may produce surface staining of the teeth
- adequate toothbrushing may prevent these stains which are not harmful or permanent and may be removed by your dentist
- this Crest is specially formulated to help prevent staining
- see your dentist regularly

Inactive ingredients

glycerin, hydrated silica, sodium hexametaphosphate, propylene glycol, PEG-6, water, zinc lactate, flavor, sodium lauryl sulfate, sodium gluconate, sodium saccharin, trisodium phosphate, carrageenan, xanthan gum, PVP, blue 1

Questions?

1-800-594-4158

DISTR. BY PROCTER & GAMBLE,
CINCINNATI, OH 45202

PRINCIPAL DISPLAY PANEL - 144 g Tube Carton

PROTECTS AGAINST AREAS DENTISTS CHECK MOST. Patented Stannous Fluoride Technology

Crest ® PRO-HEALTH™ ADVANCED

FLUORIDE TOOTHPASTE FOR ANTICAVITY, ANTIGINGIVITIS AND SENSITIVE TEETH

EXTRA WHITENING

Removes surface stains & protects against future stains.

CAVITIES GINGIVITIS ACID EROSION* SENSITIVITY PLAQUE TARTAR WHITENING FRESHENS BREATH

NET WT 5.1 OZ (144 g)